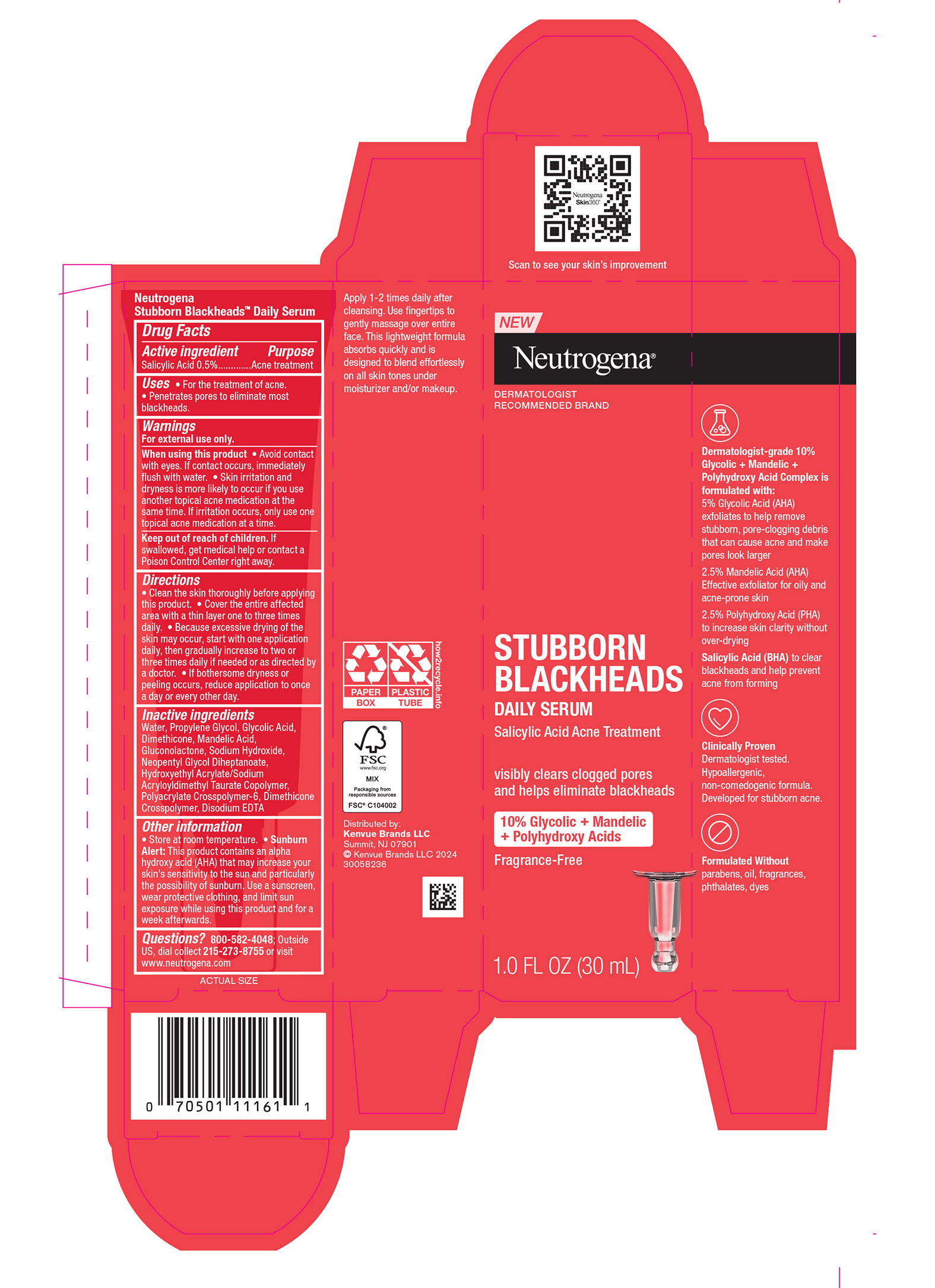 DRUG LABEL: Neutrogena Stubborn Blackheads Daily Serum
NDC: 69968-0703 | Form: LOTION
Manufacturer: Kenvue Brands LLC
Category: otc | Type: HUMAN OTC DRUG LABEL
Date: 20241126

ACTIVE INGREDIENTS: SALICYLIC ACID 5 mg/1 mL
INACTIVE INGREDIENTS: WATER; PROPYLENE GLYCOL; GLYCOLIC ACID; DIMETHICONE; MANDELIC ACID; GLUCONOLACTONE; SODIUM HYDROXIDE; NEOPENTYL GLYCOL DIHEPTANOATE; HYDROXYETHYL ACRYLATE/SODIUM ACRYLOYLDIMETHYL TAURATE COPOLYMER (100000 MPA.S AT 1.5%); AMMONIUM ACRYLOYLDIMETHYLTAURATE, DIMETHYLACRYLAMIDE, LAURYL METHACRYLATE AND LAURETH-4 METHACRYLATE COPOLYMER, TRIMETHYLOLPROPANE TRIACRYLATE CROSSLINKED (45000 MPA.S); DIMETHICONE CROSSPOLYMER (450000 MPA.S AT 12% IN CYCLOPENTASILOXANE); EDETATE DISODIUM

Neutrogena® STUBBORN BLACKHEADS DAILY SERUM

Drug Facts

Active ingredient

Salicylic Acid 0.5%

Purpose

Acne treatment

Use

- For the treatment of acne
- Penetrates pores to eliminate most blackheads.

Warnings

For external use only.

When using this product

- Avoid contact with eyes. If contact occurs, immediately flush with water.
- Skin irritation and dryness is more likely to occur if you use another topical acne medication at the same time. If irritation occurs, only use one topical acne medication at a time.

Keep out of reach of children. If swallowed, get medical help or contact a Poison Control Center right away.

Directions

- Clean the skin thoroughly before applying this product.
- Cover the entire affected area with a thin layer one to three times daily.
- Because excessive drying of the skin may occur, start with one application daily, then gradually increase to two or three times daily if needed or as directed by a doctor.
- If bothersome dryness or peeling occurs, reduce application to once a day or every other day.

Inactive ingredients

Water, Propylene Glycol, Glycolic Acid, Dimethicone, Mandelic Acid, Gluconolactone, Sodium Hydroxide, Neopentyl Glycol Diheptanoate, Hydroxyethyl Acrylate/Sodium Acryloyldimethyl Taurate Copolymer, Polyacrylate Crosspolymer-6, Dimethicone Crosspolymer, Disodium EDTA

Other information

- Store at room temperature.
- Sunburn Alert: This product contains an alpha hydroxy acid (AHA) that may increase your skin's sensitivity to the sun and particularly the possibility of sunburn. Use a sunscreen, wear protective clothing, and limit sun exposure while using this product and for a week afterwards.

Questions?

800-582-4048; Outside US, dial collect 215-273-8755 or visit www.neutrogena.com

Distributed by:
Kenvue Brands LLC
Summit, NJ 07901

PRINCIPAL DISPLAY PANEL - 30 mL Tube Carton

New
Neutrogena®
DERMATOLOGIST
RECOMMENDED BRAND

STUBBORN
BLACKHEADS
DAILY SERUM
Salicylic Acid Acne Treatment

visibly clears clogged pores
and helps eliminate blackheads

10% Glycolic + Mandelic
+ Polyhydroxy Acids
Fragrance-Free

1.0 FL OZ (30mL)